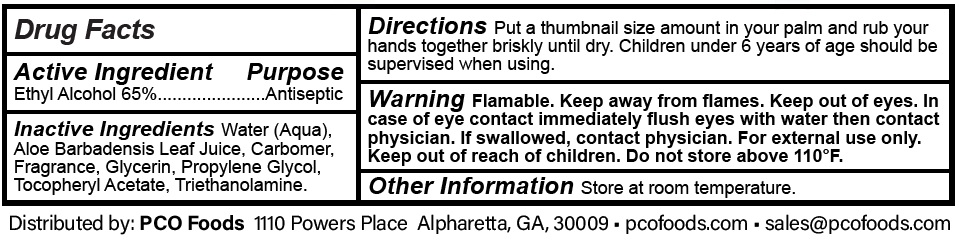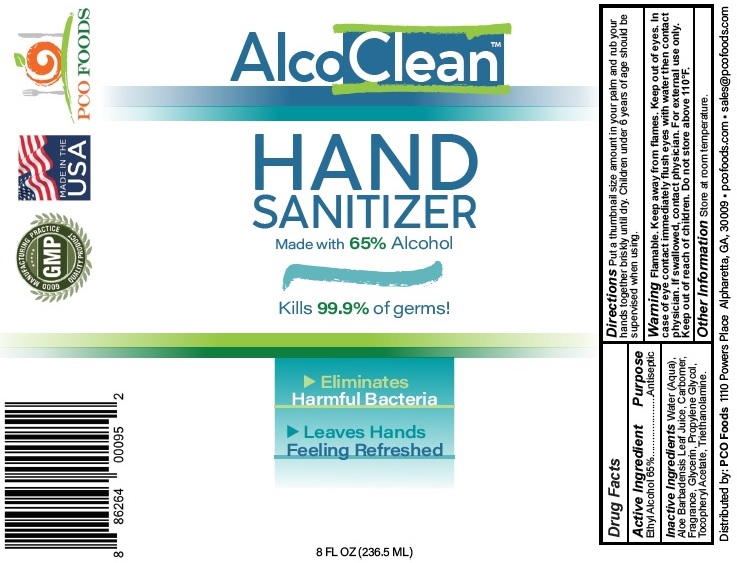 DRUG LABEL: AlcoClean Hand Sanitizer
NDC: 53113-095 | Form: GEL
Manufacturer: GADAL Laboratories, Inc
Category: otc | Type: HUMAN OTC DRUG LABEL
Date: 20200724

ACTIVE INGREDIENTS: ALCOHOL 65 mL/100 mL
INACTIVE INGREDIENTS: WATER; ALOE VERA LEAF; CARBOMER HOMOPOLYMER, UNSPECIFIED TYPE; GLYCERIN; PROPYLENE GLYCOL; .ALPHA.-TOCOPHEROL ACETATE; TROLAMINE

AlcoClean HAND SANITIZER

Active Ingredient

Ethyl Alcohol 65%

Purpose

Antiseptic

Uses

• hand sanitizer to decrease bacteria on the skin
• recommended for repeated use
• for use when soap and water are not available

Inactive Ingredients

Water (Aqua), Aloe Barbadensis Leaf Juice, Carbomer, Fragrance, Glycerin, Propylene Glycol, Tocopheryl Acetate, Triethanolamine.

Directions

Put a thumbnail size amount in your palm and rub your hands together briskly until dry. Children under 6 years of age should be supervised when using.

Warning

Flammable. Keep away from flames. Keep out of eyes. In case of eye contact immediately flush eyes with water then contact physician. If swallowed, contact physician. For external use only. Do not store above 110°F.

Other Information

Store at room temperature.

Made with 65% Alcohol

Kills 99.9% of germs!

Eliminates Harmful Bacteria
Leaves Hands Feeling Refreshed

GOOD MANUFACTURING PRACTICE

GMP

QUALITY PRODUCT

MADE IN THE USA

PCO FOODS

Distributed by: PCO Foods 1110 Powers Place Alpharetta, GA, 30009 • pcofoods.com • sales@pcofoods.com